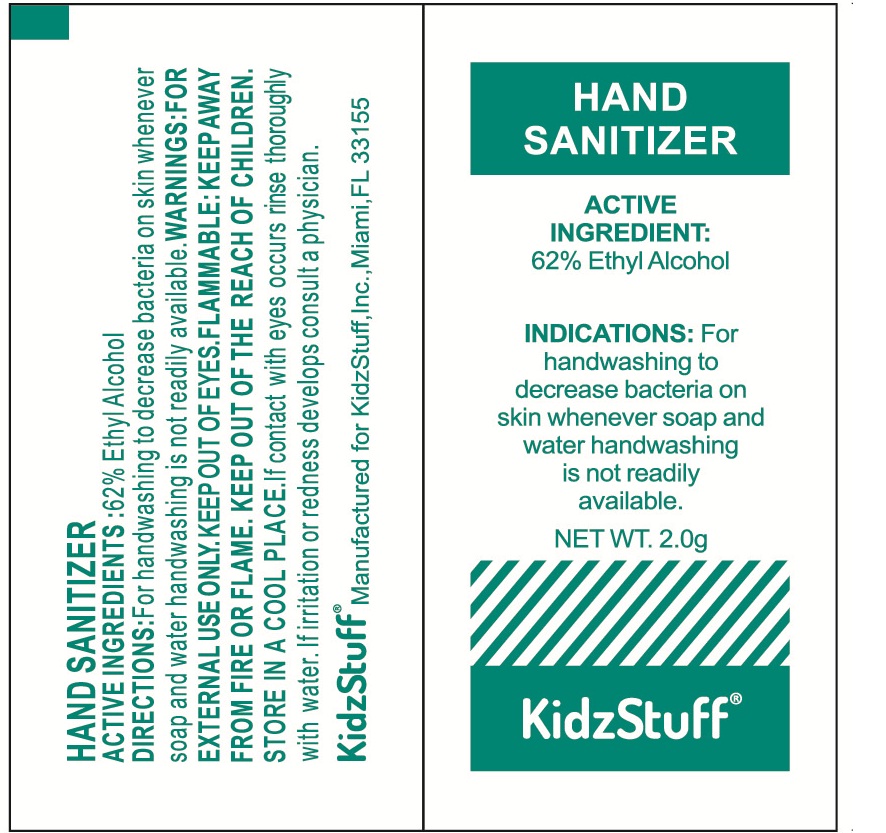 DRUG LABEL: KidzStuff Hand Sanitizer
NDC: 71734-204 | Form: LIQUID
Manufacturer: JIANGMEN SHUIZIRUN SANITARY ARTICLES CO., LTD.
Category: otc | Type: HUMAN OTC DRUG LABEL
Date: 20180117

ACTIVE INGREDIENTS: ALCOHOL 62 g/100 g
INACTIVE INGREDIENTS: ALOE VERA LEAF; GLYCERIN; PROPYLENE GLYCOL; TOCOPHEROL; TROLAMINE; WATER

Drug Fact

Active Ingredient

Ethyl Alcohol 62%

Purpose

antiseptic

Uses

- to decrease bacteria on the skin that could cause disease
- recommended for repeated use

Warnings

For external use only- hands.

Flammable. Keep away from heat and flame.

When using this product, keep out of eyes. In case of contact with eyes, flush thoroughly with water.

Avoid contact with broken skin.

Do not inhale or ingest.

Stop use and ask a doctor if skin irritation develops.

When using this product

- keep out of eyes. In case of contact with eyes, immediately flush with water and call a doctor.
- avoid contact with broken skin.

Stop use and ask a doctor

if irritation or redness develops

Keep out of reach of children.

In case of accidental ingestion, seek professional assistance or contact a Poison Control Center immediately.

Directions

- wet hands thoroughly with product and allow to dry without wiping
- for children under 6, use only under adult supervision
- not recommended for infants

Inactive Ingredients

purified water, glycerin, triethanolamine, carbomer, aloe essence